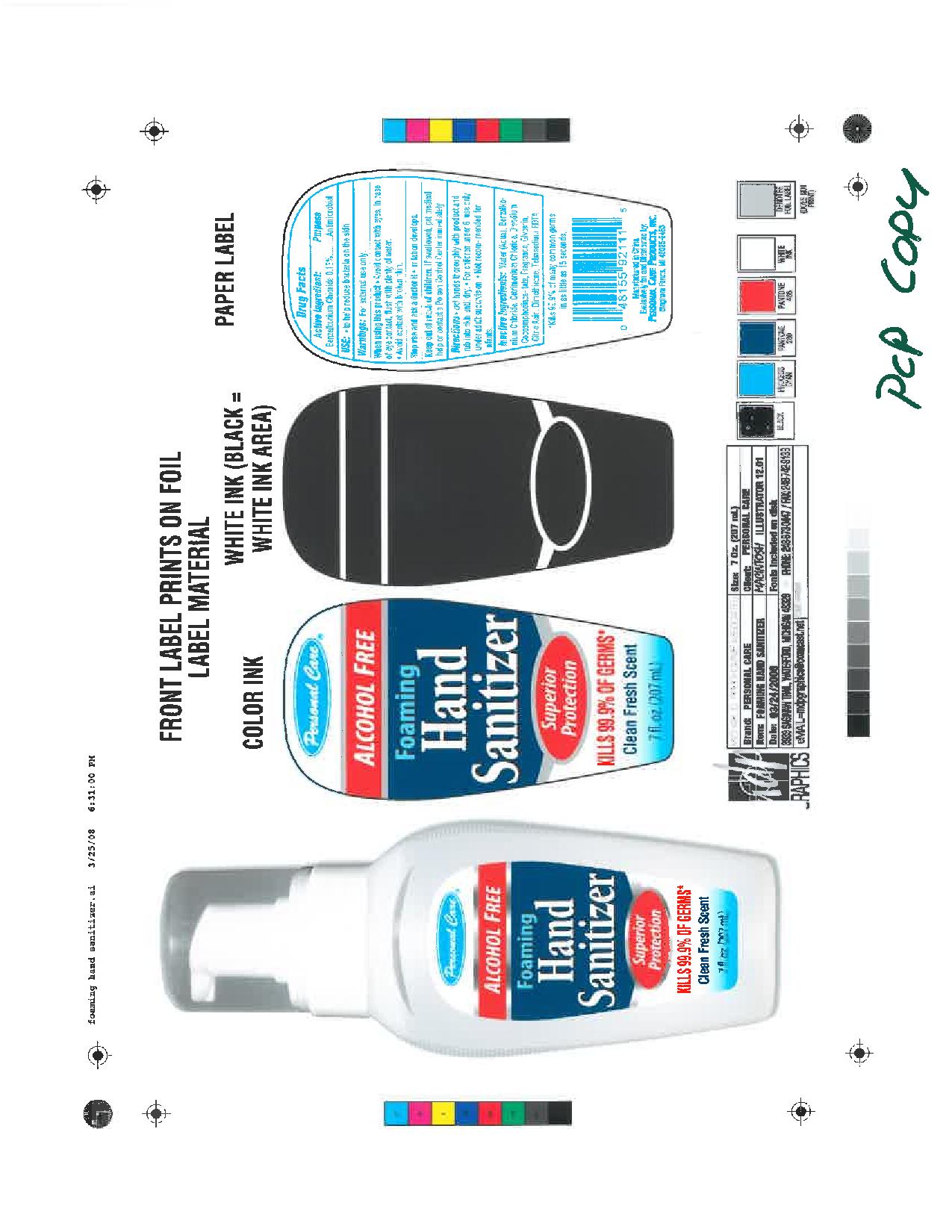 DRUG LABEL: Hand Sanitizer
                        
NDC: 29500-9088 | Form: AEROSOL, FOAM
Manufacturer: Personal Care Products
Category: otc | Type: HUMAN OTC DRUG LABEL
Date: 20111230

ACTIVE INGREDIENTS: BENZALKONIUM CHLORIDE .27 mL/207 mL
INACTIVE INGREDIENTS: WATER; DISODIUM COCOAMPHODIACETATE; GLYCERIN; CITRIC ACID; DIMETHICONE; EDETATE SODIUM

Hand Sanitizer

Active Ingredient

Benzalkonium Chloride

Purpose

Antimicrobial

Keep out of reach of children. If swallowed, get medical help or contact a Poison Control Center immediately.

Warnings:

For external use only.

When using this product: Avoid contact with eyes. In case of eye contact, flush with plenty of water. Avoid contact with broken skin.

Stop use and ask a doctor if irritation develops.

Directions:

Wet hands thoroughly with product and rub into skin until dry.

For children under 6, use only under adult supervision.

Not recommended for infants.

Inactive Ingredients
Water(Aqua), Benzalkoinum chloride, cetrimonium chloride, disodium cocoamphodicetate, fragrance, glycerin, citric acid, dimethicone, tetrasodium EDTA

INDICATIONS AND USAGE

Use: To reduce bacteria on the skin.

PACKAGE LABEL

Personal Care

Alcohol Free

Foaming Hand Sanitizer

Superior protection

Kills 99.9% of germs*

Clean Fresh Scent

7 fl oz (207 ml)